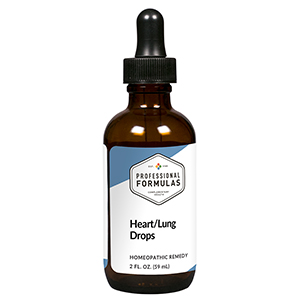 DRUG LABEL: Heart/Lung Drops
NDC: 63083-5007 | Form: LIQUID
Manufacturer: Professional Complementary Health Formulas
Category: homeopathic | Type: HUMAN OTC DRUG LABEL
Date: 20190815

ACTIVE INGREDIENTS: FERROSOFERRIC PHOSPHATE 6 [hp_X]/59 mL; BEEF HEART 6 [hp_X]/59 mL; BEEF LUNG 6 [hp_X]/59 mL; DIGITALIS 12 [hp_X]/59 mL; LACHESIS MUTA VENOM 12 [hp_X]/59 mL
INACTIVE INGREDIENTS: ALCOHOL; WATER

HHL

ACTIVE INGREDIENTS

Ferrum phosphoricum 6X
Heart 6X, 12X, 30X, 60X, 100X
Lung 6X, 12X, 30X, 60X, 100X
Digitalis purpurea 12X
Lachesis mutus 12X

QUESTIONS

Professional Formulas

PO Box 2034 Lake Oswego, OR 97035

INDICATIONS

For the temporary relief of shortness of breath, wheezing, mild chest tightness, cough, or lack of energy.*

PURPOSE

*Claims based on traditional homeopathic practice, not accepted medical evidence. Not FDA evaluated.

WARNINGS

Severe or persistent symptoms may be serious. Consult a doctor promptly. Keep out of the reach of children. In case of overdose, get medical help or contact a poison control center right away. If pregnant or breastfeeding, ask a healthcare professional before use.

Keep out of the reach of children.

PREGNANCY OR BREAST FEEDING

If pregnant or breastfeeding, ask a healthcare professional before use.

DIRECTIONS

Place drops under tongue 30 minutes before/after meals. Adults and children 12 years and over: Take 10 drops up to 3 times per day. Consult a physician for use in children under 12 years of age.

OTHER INFORMATION

Tamper resistant. If seal is broken, do not use. After opening, close container tightly and store at room temperature away from heat.

INACTIVE INGREDIENTS

20% ethanol, purified water.

LABEL

Est 1985

Professional Formulas

Complementary Health

Heart/Lung Drops

Homeopathic Remedy

2 FL. OZ. (59 mL)